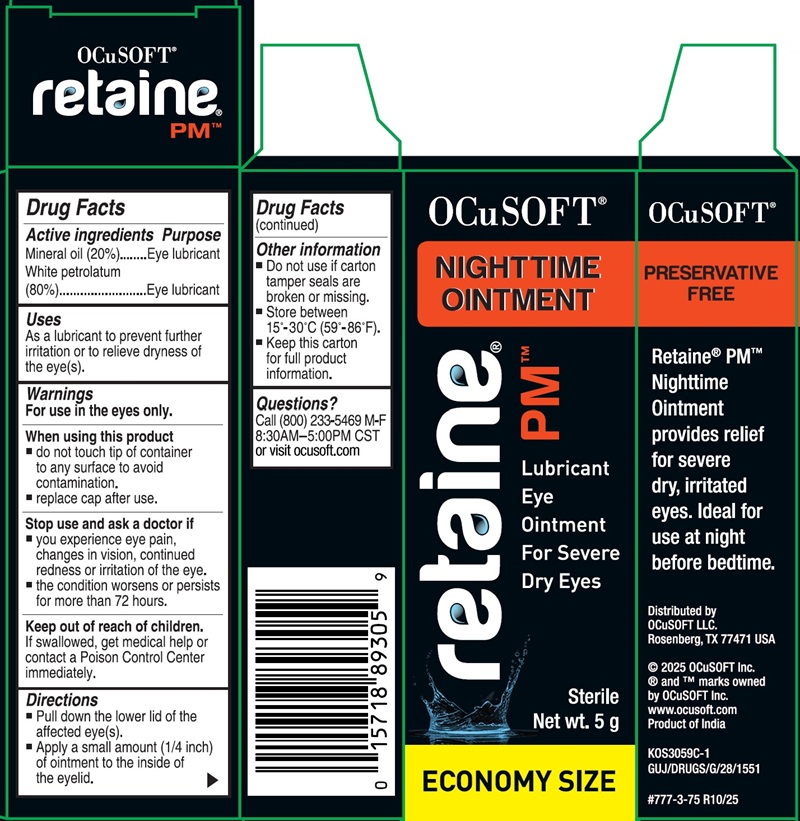 DRUG LABEL: retaine PM
NDC: 54799-893 | Form: OINTMENT
Manufacturer: OCuSOFT LLC
Category: otc | Type: HUMAN OTC DRUG LABEL
Date: 20260115

ACTIVE INGREDIENTS: Mineral Oil 200 mg/1 g; Petrolatum 800 mg/1 g

Retaine PM

Active ingredients

Mineral oil (20%)
White petrolatum (80%)

Purpose

Eye lubricant

Uses

As a lubricant to prevent further irritaion or to relieve dryness of the eye(s).

Warnings

For use in the eyes only.

When using this product

● do not touch tip of container to any surface to avoid contamination.
● replace cap after use.

Stop use and ask a doctor if

● you experience eye pain, changes in vision, continued redness or irritation of the eye.
● the condition worsens or persists for more than 72 hours.

Keep out of reach of children.

If swallowed, get medical help or contact a Poison Control Center immediately.

Directions

● Pull down the lower lid of the affected eye(s).
● Apply a small amount (1/4 inch) of ointment to the inside of the eyelid.

Inactive Ingredients

None

Other information

● Do not use if cap breakaway seal is broken or missing.
● Store between 15°-30°C (59°-86°F).
● Keep this carton for full product information.

Questions?

Call (800) 233-5469 M-F
8:30AM-5:00PM CST
or visit ocusoft.com

Package label. Principal Display Panel

OCuSOFT®
NIGHTTIME
OINTMENT
retaine
PM™
Lubricant
Eye
Ointment
For Severe
Dry Eyes
Sterile
Net wt. 5 g
ECONOMY SIZE
PRESERVATIVE
FREE
Retaine® PM™
Nighttime
Ointment
provides relief
for severe
dry, irritated
eyes. Ideal for
use at night
before bedtime.
Distributed by
OCuSOFT LLC.
Rosenberg, TX 77471 USA
© 2025 OCuSOFT Inc.
® and ™ marks owned
by OCuSOFT Inc.
www.ocusoft.com
Product of India
K0S3059C-1
GUJ/DRUGS/G/28/1551
#777-3-75 R10/25